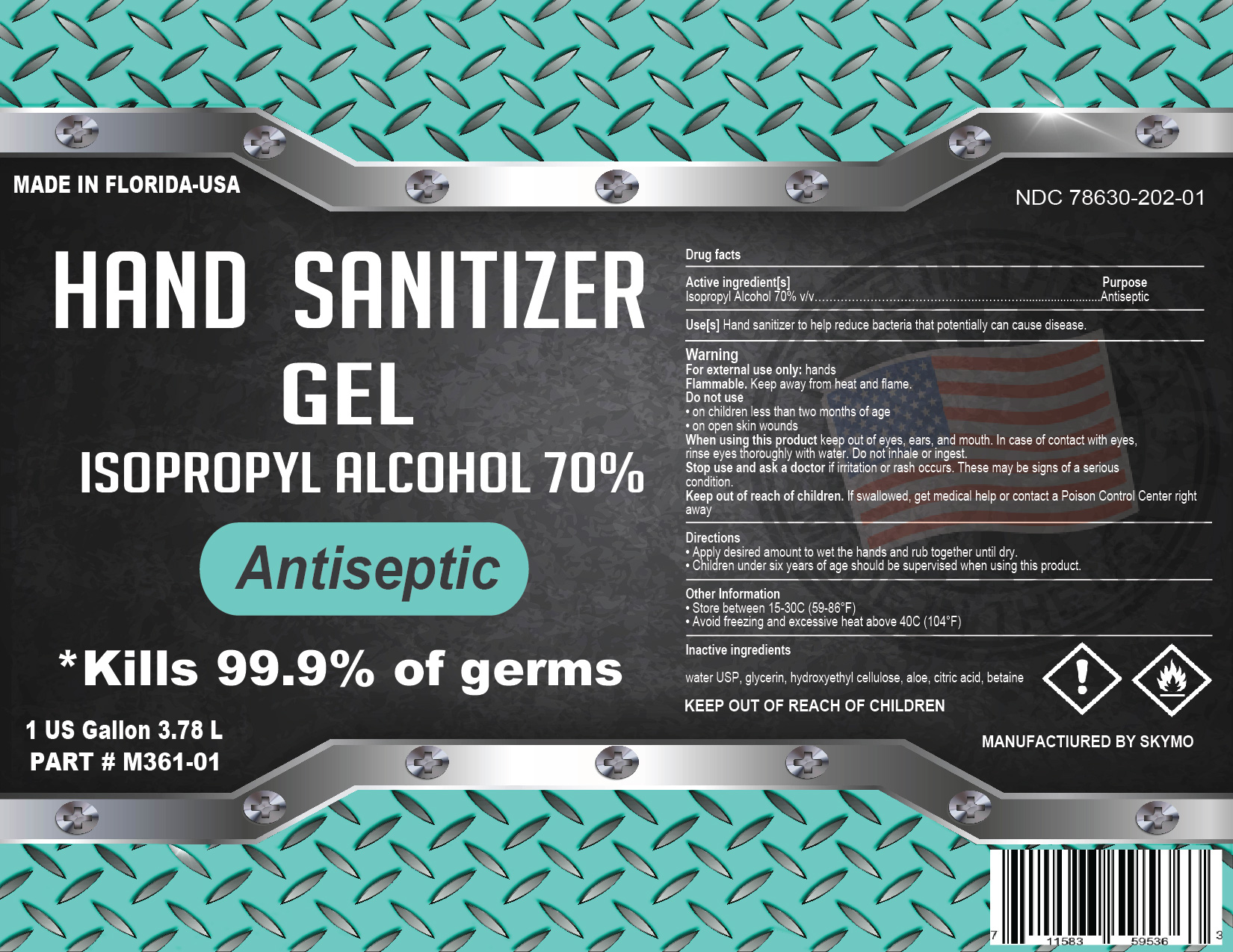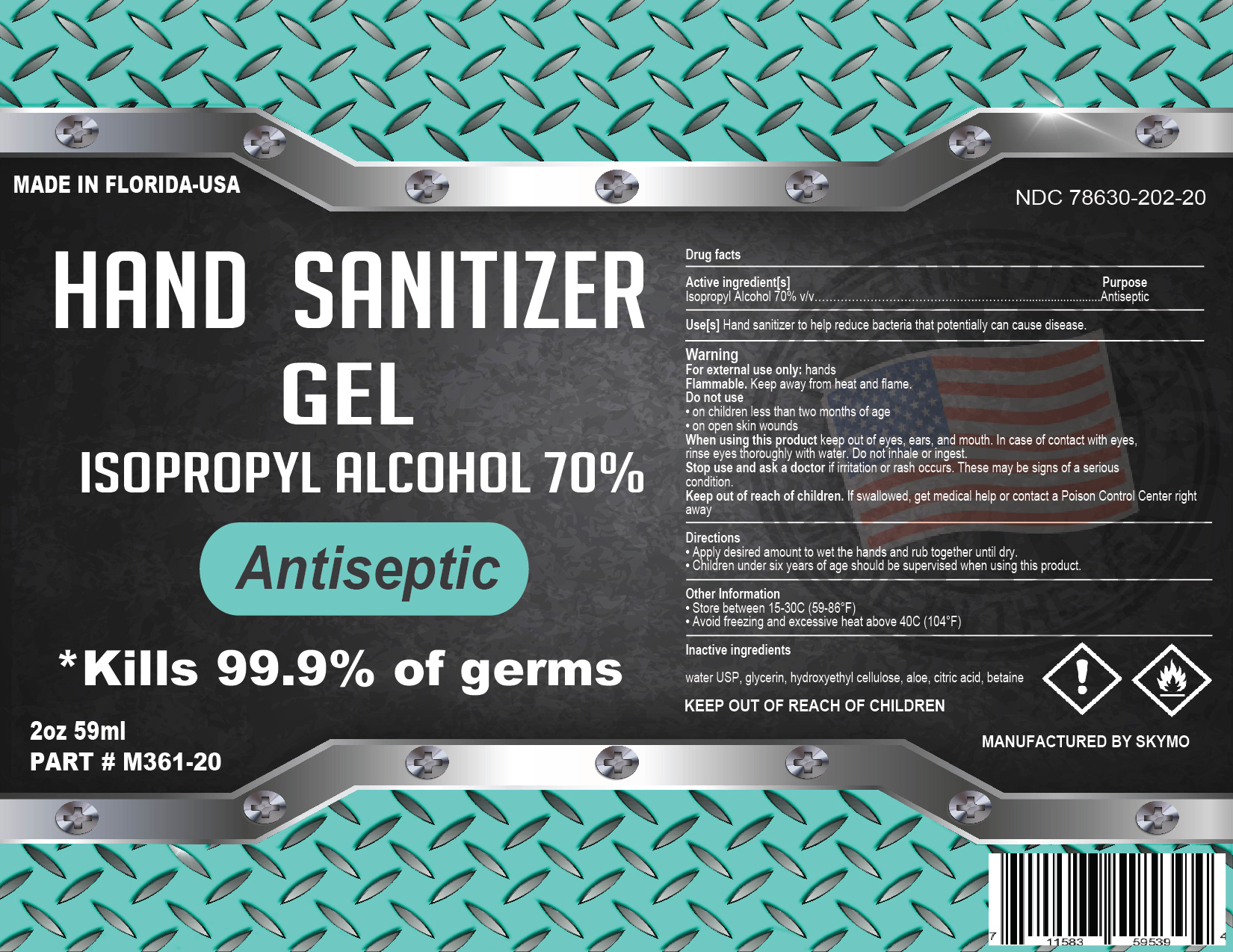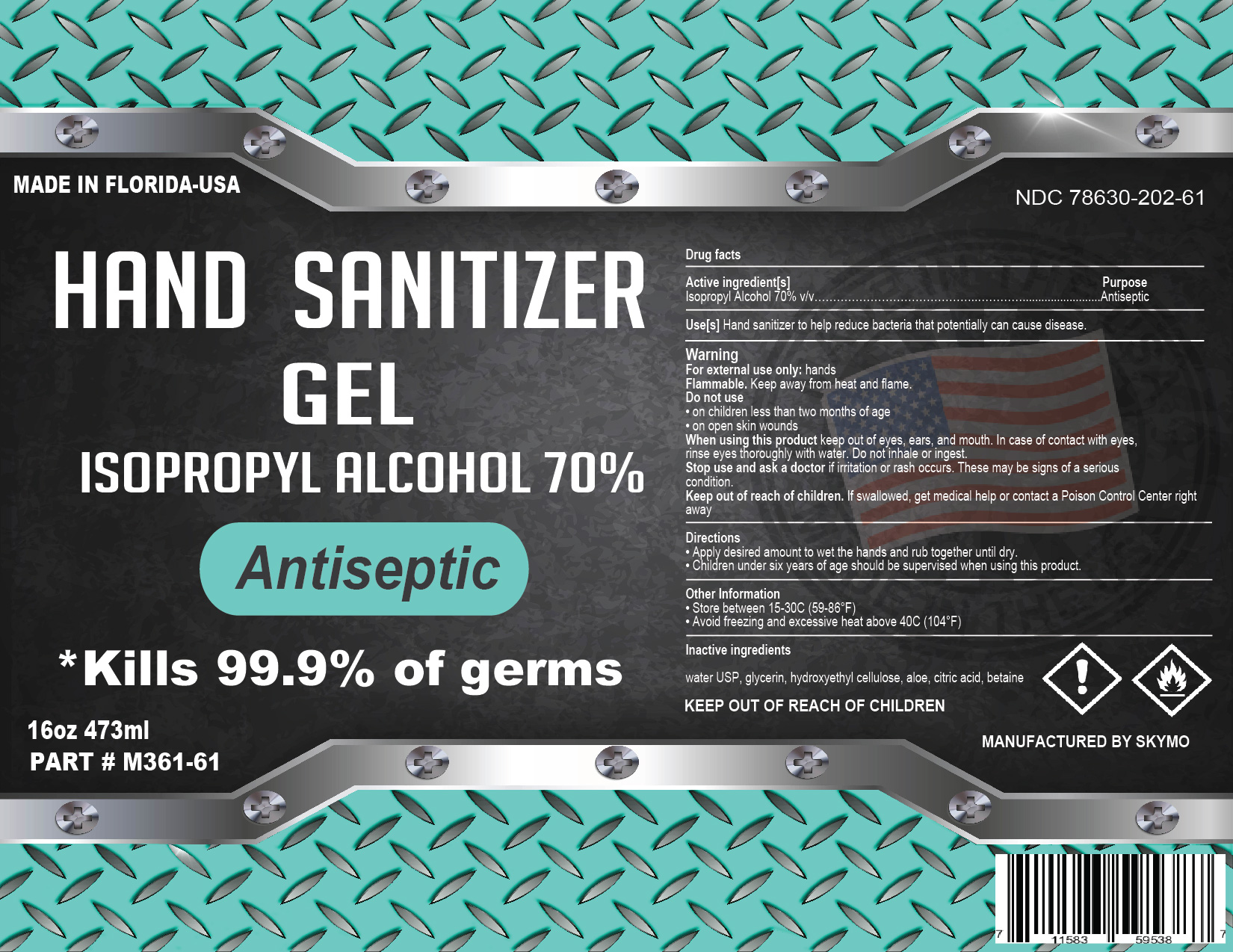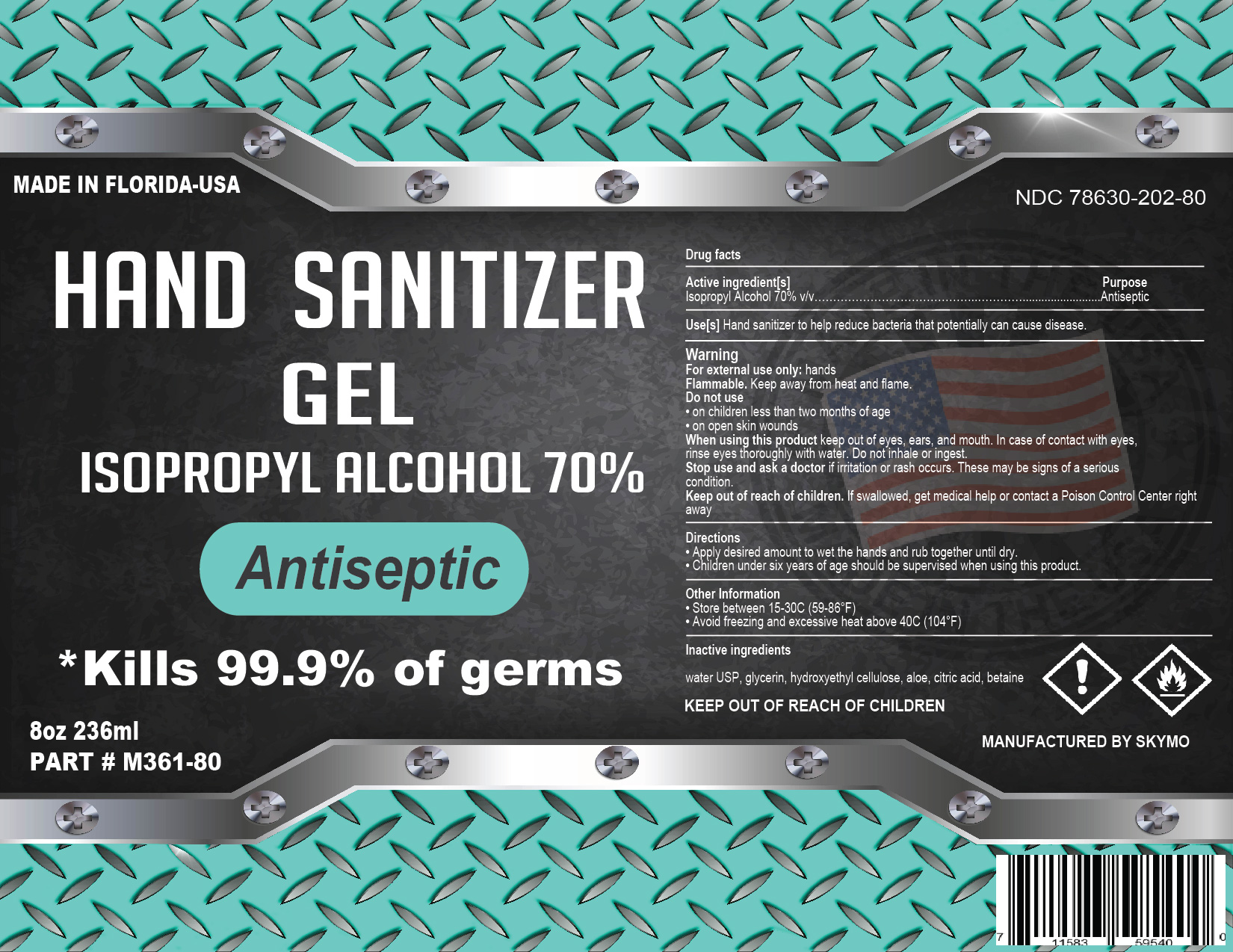 DRUG LABEL: SKYMO Hand Sanitizer
NDC: 78630-202 | Form: LIQUID
Manufacturer: SKYMO
Category: otc | Type: HUMAN OTC DRUG LABEL
Date: 20231002

ACTIVE INGREDIENTS: ISOPROPYL ALCOHOL 70 mL/100 mL
INACTIVE INGREDIENTS: GLYCERIN 1.45 mL/100 mL; BETAINE; WATER; ALOE VERA LEAF; CITRIC ACID MONOHYDRATE; HYDROXYETHYL CELLULOSE (2000 CPS AT 1%)

This is a hand sanitizer manufactured according to the Temporary Policy for Preparation of Certain Alcohol-Based Hand Sanitizer Products During the Public Health Emergency (CoViD-19); Guidance for Industry.

The hand sanitizer is manufactured using only the following United States Pharmacopoeia (USP) grade ingredients in the preparation of the product (percentage in final product formulation) consistent with World Health Organization (WHO) recommendations:

Active Ingredient(s)

Isopropyl Alcohol 70% v/v. Purpose: Antiseptic

Purpose

Antiseptic, Hand Sanitizer

Use

Hand Sanitizer to help reduce bacteria that potentially can cause disease. For use when soap and water are not available.

Warnings

For external use only. Flammable. Keep away from heat or flame

Do not use

- in children less than 2 months of age
- on open skin wounds

When using this product keep out of eyes, ears, and mouth. In case of contact with eyes, rinse eyes thoroughly with water.
Stop use and ask a doctor if irritation or rash occurs. These may be signs of a serious condition.
Keep out of reach of children. If swallowed, get medical help or contact a Poison Control Center right away.

Stop use and ask a doctor if irritation or rash occurs. These may be signs of a serious condition.

Keep out of reach of children. If swallowed, get medical help or contact a Poison Control Center right away.

Directions

- Place enough product on hands to cover all surfaces. Rub hands together until dry.
- Supervise children under 6 years of age when using this product to avoid swallowing.

Other information

- Store between 15-30C (59-86F)
- Avoid freezing and excessive heat above 40C (104F)

Inactive ingredients

water USP, glycerin, hydroxyethyl cellulose, aloe, citric acid, betaine

Package Label - Principal Display Panel

NDC: 78630-202-61

NDC: 78630-202-01

NDC: 78630-202-80

NDC: 78630-202-20